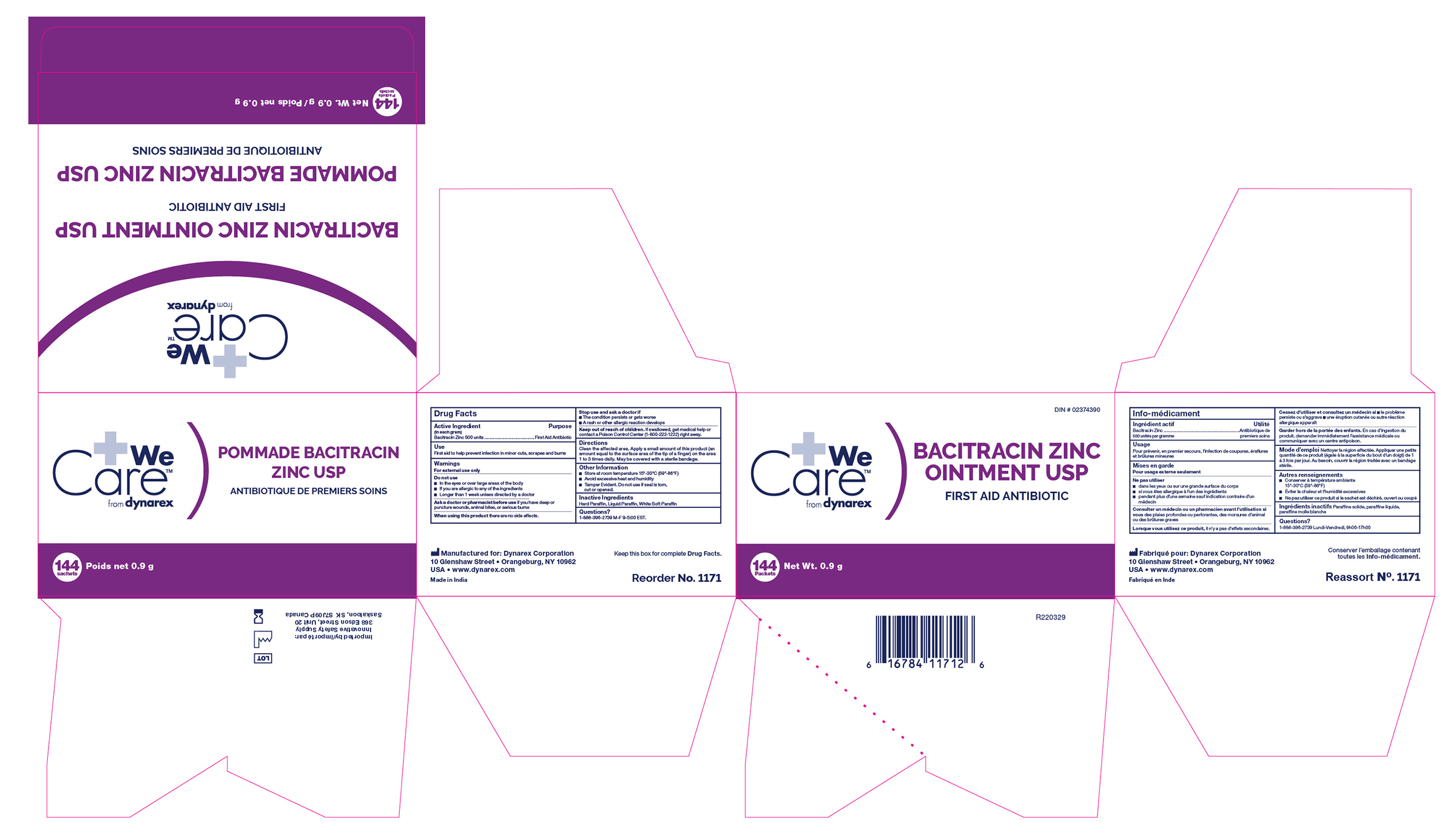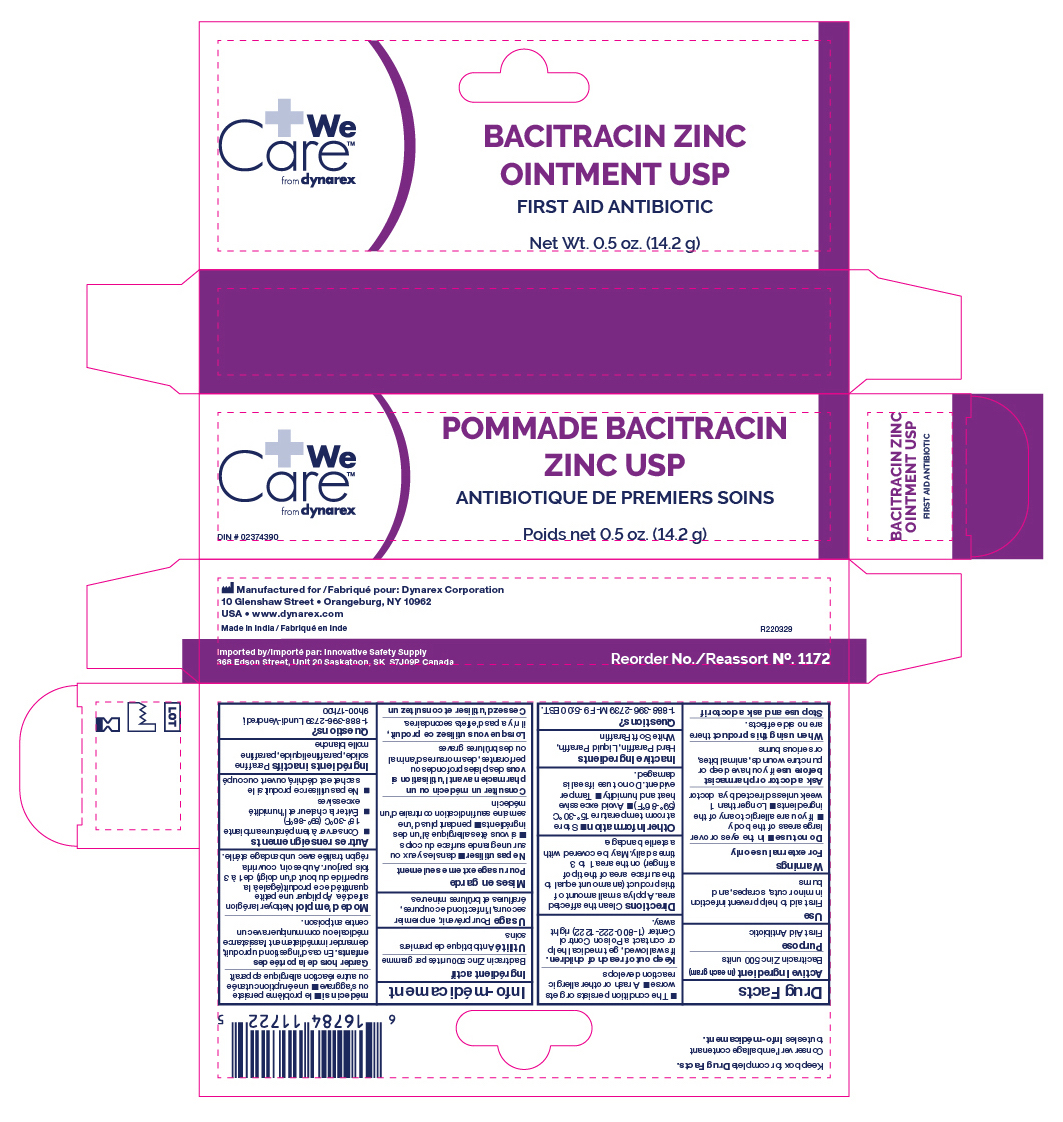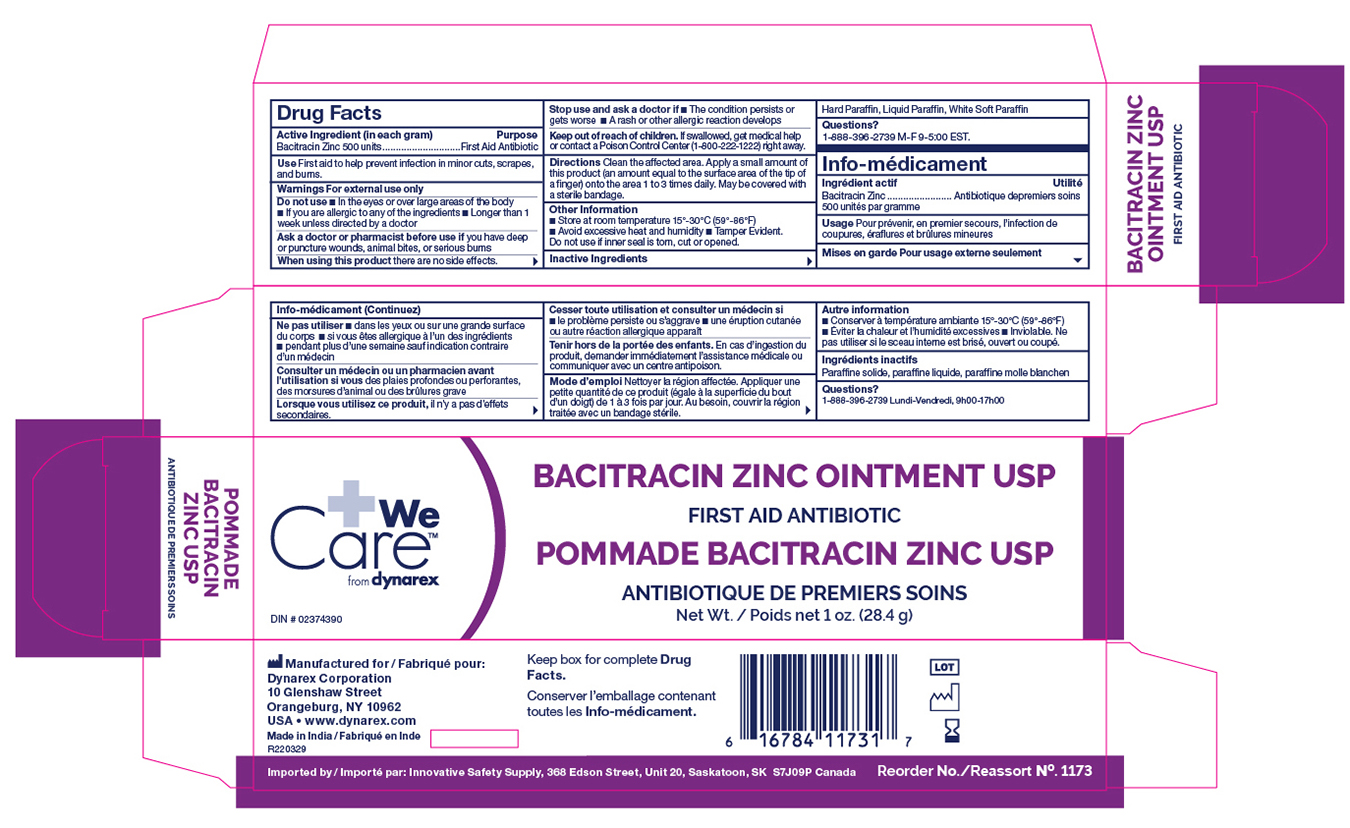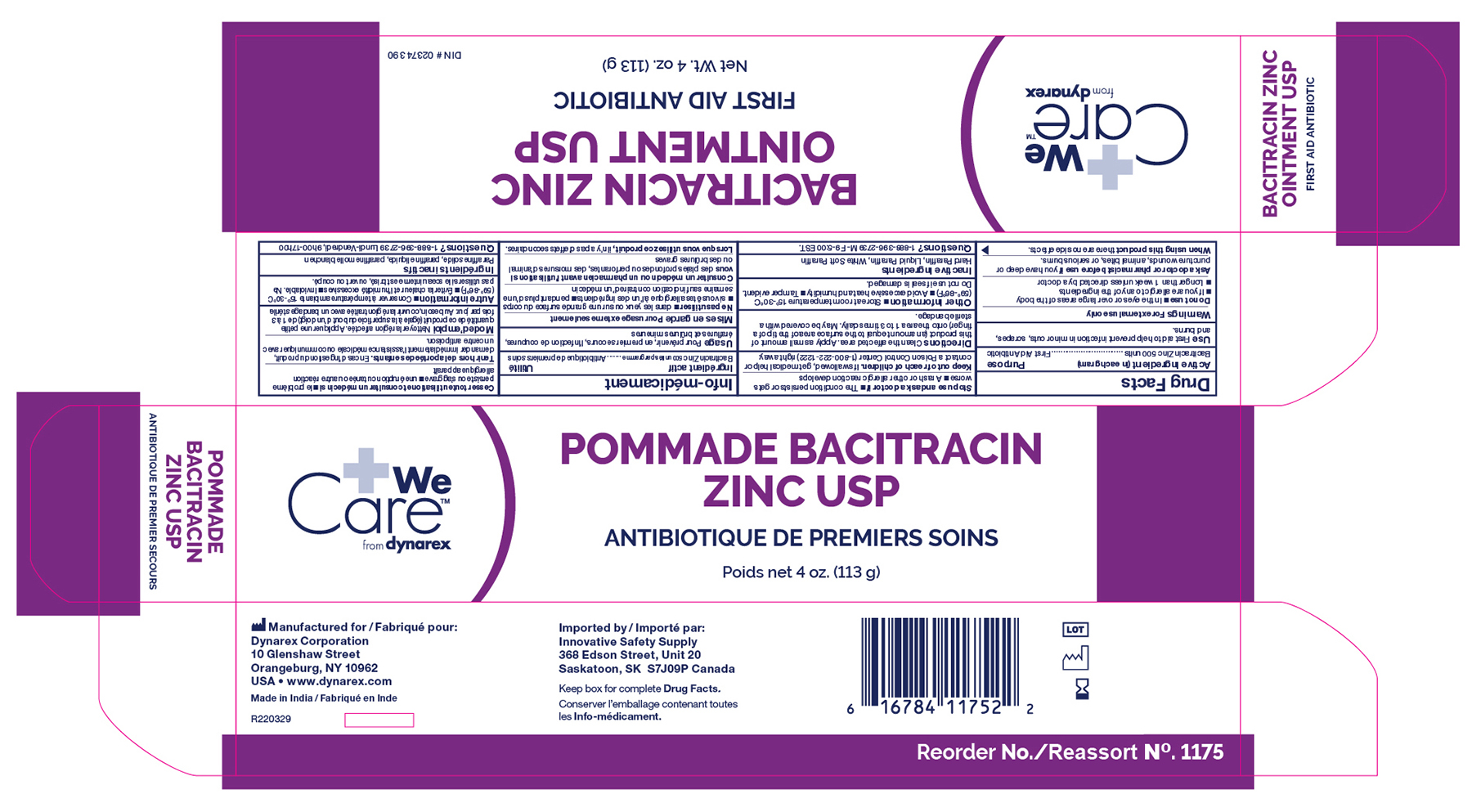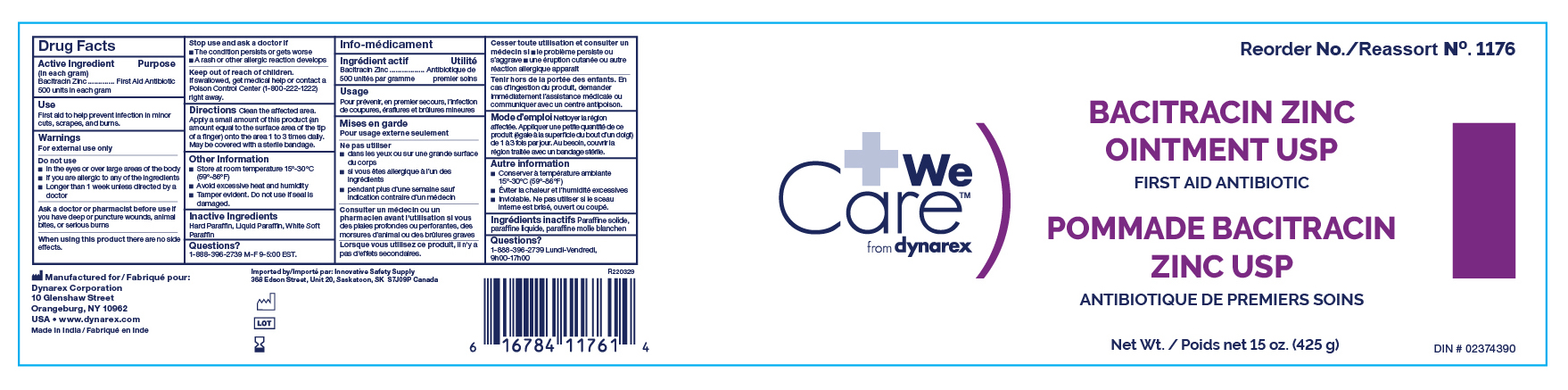 DRUG LABEL: Bacitracin Zinc
NDC: 67777-008 | Form: OINTMENT
Manufacturer: Dynarex Corporation
Category: otc | Type: HUMAN OTC DRUG LABEL
Date: 20250616

ACTIVE INGREDIENTS: BACITRACIN ZINC 500 [USP'U]/1 g
INACTIVE INGREDIENTS: MINERAL OIL; WHITE PETROLATUM; PARAFFIN

1171 Bacitracin Zinc Ointment NDC 67777-008-10
1172 Bacitracin Zinc Ointment NDC 67777-008-20
1173 Bacitracin Zinc Ointment NDC 67777-008-30
1175 Bacitracin Zinc Ointment NDC 67777-008-50
1176 Bacitracin Zinc Ointment NDC 67777-008-60

Active Ingredient

Bacitracin Zinc (500 units in each gram)

Purpose

First Aid Antibiotic

Uses

First aid to help prevent infection in minor cuts, scrapes, and burns

Warnings

For external use only

Do not use

- In the eyes or apply over large areas of the body
- If you are allergic to any of the ingredients
- Longer than 1 week unless directed by a doctor

Ask a doctor before use if you have

deep or puncture wounds, animal bites, or serious burns

Stop use and ask a doctor if

the condition persists or gets worse, or if a rash or other allergic reaction develops

KEEP OUT OF REACH OF CHILDREN

If swallowed, get medical help or contact a Poison Control Center right away.

Directions

Clean the affected area. Apply a small amount of this product (an amount equal to the surface area of the tip of a finger) on the area 1 to 3 times daily. May be covered with a sterile bandage.

Other Information

- Store at room temperature
- Avoid excessive heat and humidity
- Tamper Evident. Do not use if inner seal is torn, cut or opened.

Inactive Ingredients

Hard Paraffin, Liquid Paraffin, White Soft Paraffin

1172 Label

1172 Bacitracin Zinc

1173 Label

1173 Bacitracin Zinc

1175 Label

1175 Bacitracin Zinc

1171 Label

1171 Bacitracin Zinc